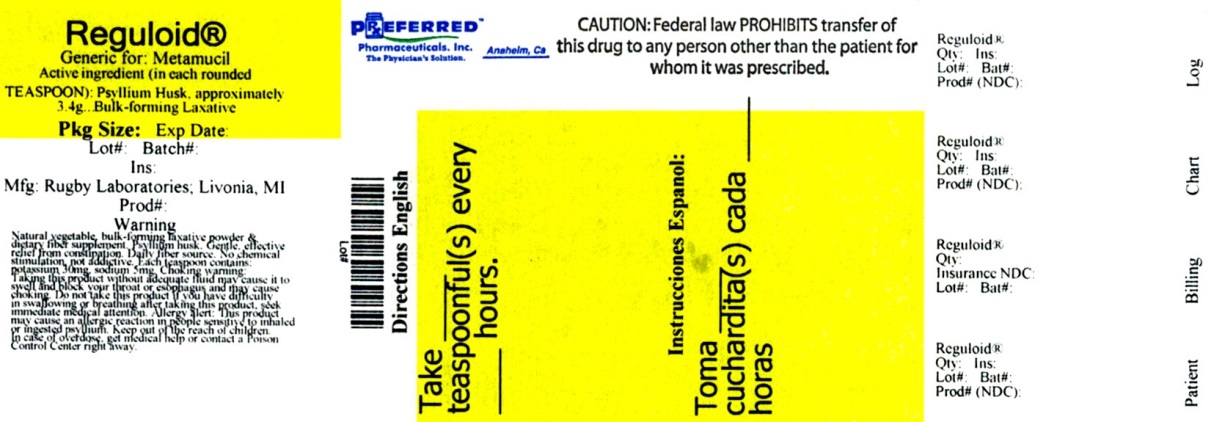 DRUG LABEL: Reguloid
NDC: 68788-7129 | Form: POWDER, FOR SOLUTION
Manufacturer: Preferred Pharmaceuticals Inc.
Category: otc | Type: HUMAN OTC DRUG LABEL
Date: 20180330

ACTIVE INGREDIENTS: PSYLLIUM HUSK 3.4 g/7 g
INACTIVE INGREDIENTS: SUCROSE

2688 - Rugby

Drug Facts

Active ingredient (in each rounded TEASPOON)

Psyllium Husks, approximately 3.4 g

Purpose

Bulk-forming Laxative

Uses

relieves occasional constipation
generally produces bowel movement in 12-72 hours

Warnings

Choking: Taking this product without adequate fluid may cause it to swell and block your throat or esophagus and may cause choking. Do not take this product if you have difficulty in swallowing. If you experience chest pain, vomiting, or difficulty in swallowing or breathing after taking this product, seek immediate medical attention.

Allergy alert: This product may cause an allergic reaction in people sensitive to inhaled or ingested psyllium

Ask a doctor before use if you have

• a sudden change in bowel habits persisting for 2 weeks

• abdominal pain, nausea, or vomiting

Ask a doctor or pharmacist before use if you are

taking any other drug. Take this product two or more hours before or after other drugs. Laxatives may affect how other drugs work.

Stop use and ask a doctor if

• constipation lasts more than 7 days

• rectal bleeding occurs

These may be signs of a serious condition.

OVERDOSAGE

In case of overdose, get medical help or contact a Poison Control Center right away.

Directions

• put one dose into an empty glass

• mix this product (child or adult dose) with at least 8 ounces (oz) (a full glass) of water or other fluid. Taking this product without enough liquid may cause choking. See choking warning.

• stir briskly and drink promptly. If mixture thickens, add more liquid and stir.

adults & children 12 years & over | 1 rounded TEASPOON in 8 oz of liquid,; up to 3 times daily
children 6 to under 12 years | 1/2 adult dose in 8 oz of liquid, up to 3 times daily
children under 6 years | ask a doctor

New Users : Start with one dose per day, gradually increase to 3 doses per day as necessary.

As your body adjusts to increased fiber intake, you may experience changes in bowel habits or minor bloating.

Other information

each teaspoon contains: potassium 30 mg, sodium 5 mg

Inactive ingredient

sucrose

Questions or comments?

1-800-645-2158

DIETARY FIBER SUPPLEMENT

Diets low in saturated fat and cholesterol that include 7 grams of soluble fiber per day from psyllium husk, as in Reguloid, may reduce the risk of heart disease by lowering cholesterol. One adult dose of Reguloid has 2.4 grams of this soluble fiber. Consult a doctor if you are considering use of this product as part of a cholesterol-lowering program.

SEE WARNINGS & DIRECTIONS IN LAXATIVE SECTION.

Dosage: Adults and children 12 years and over: 1 rounded teaspoon in 8 ounces of liquid, 3 times daily. Children under 12 years: ask a doctor.

Supplement Facts
Serving Size 1 rounded teaspoon (7g)
Servings per container 77
Amount Per Serving %DV**
Calories 25
Total Carbohydrates 7 g | 2%
Dietary Fiber 3 g | 12%
Soluble Fiber 2 g | *
Sugars 3 g | *
Iron 0.4 mg | 2%
Sodium 5 mg | <1%
Potassium 30 mg | <1%
**% Daily Value (DV) is based on a 2,000 calorie diet.
*Daily Value (DV) not established.

INGREDIENTS: Sucrose, Psyllium Husk

TAMPER EVIDENT: DO NOT USE IF IMPRINTED

INNER FOIL SEAL IS BROKEN OR MISSING

Store below 30ºC (86ºF). Protect contents from humidity. Keep tightly closed.

Distributed by:

Rugby Laboratories

17177 N Laurel Park Drive

Suite 233

Livonia, MI 48152

www.rugbylaboratories.com

Re-order No. 370160

Rev. 08/17 R-29

6879-08-17

Relabeled By: Preferred Pharmaceuticals Inc.

PACKAGE LABEL

Rugby®

NDC 68788-7129-3

REGULAR FLAVOR

Reguloid®

NATURAL VEGETABLE BULK-FORMING LAXATIVE POWDER & DIETARY FIBER SUPPLEMENT

PSYLLIUM HUSK

- Gentle, Effective Relief From Constipation
- Daily Fiber Source
- No Chemical Stimulants, Not Addictive

Net Wt. 19 oz

(540 g)

Relabeled By: Preferred Pharmaceuticals Inc.